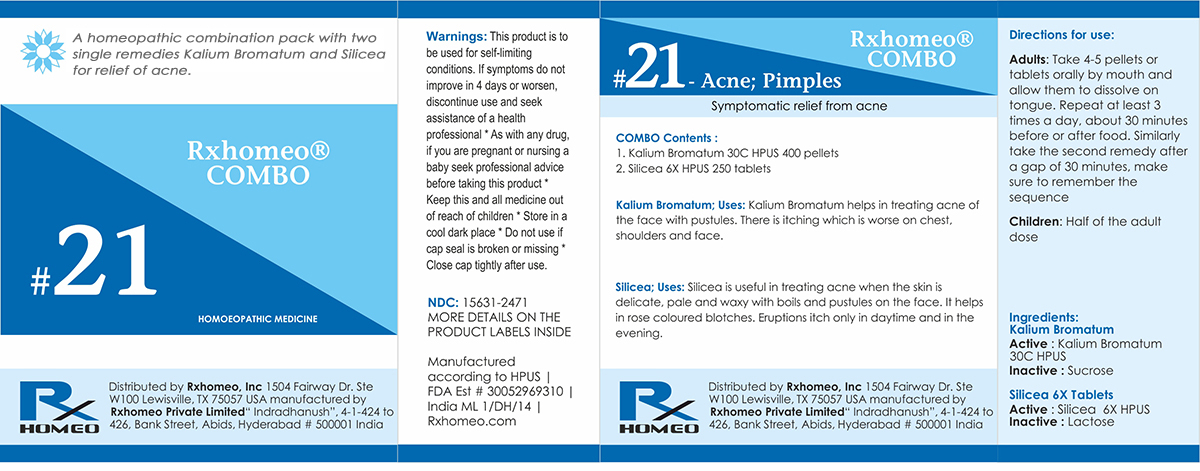 DRUG LABEL: Rxhomeo Homeopathic Combo 21
NDC: 15631-2471 | Form: KIT | Route: ORAL
Manufacturer: Rxhomeo Private Limited d.b.a.
Category: homeopathic | Type: HUMAN OTC DRUG LABEL
Date: 20161024

ACTIVE INGREDIENTS: POTASSIUM BROMIDE 1 [hp_X]/1 1; SILICON DIOXIDE 2 [hp_X]/1 1
INACTIVE INGREDIENTS: SUCROSE; LACTOSE

ACTIVE INGREDIENT

KALI BROMATUM HPUS 2X and higher

SILICEA HPUS 1X and higher

USES

A homeopathic combination pack with two single remedies Kali Bromatum and Silicea for relief of acne.

Kali Bromotum: Kali Bromatum helps in treating acne of the face with pustules. There is itching which is worse on chest, shoulders, and face.

Silicea: Silicea is useful in treating acne when the skin is delicate, pale and waxy with boils and pustules on the face. It helps in rose colored blotches. Eruptions itch only in daytime and in the evening.

INDICATIONS

Condition listed above or as directed by the physician

DOSAGE

Adults: Take 4-5 pellets or tablets orally by mouth and allow them to dissolve on tongue. Repeat at least 3 times a day, about 30 minutes before or after food. Similarly take the second remedy after a gap of 30 minutes, make sure to remember the sequence.

Children: Half of the adult dose.

WARNINGS

This product is to be used for self-limiting conditions

STOP USE

If symptoms do not improve in 4 days, or worsen, discontinue use and seek assistance of health professional

KEEP OUT OF REACH OF CHILDREN

Keep this and all medication out of reach of children

Do not use if capseal is broken or missing.

Close the cap tightly after use.

INACTIVE INGREDIENTS

Sucrose for Pellets.

Lactose for Tablets.

STORAGE

Store in a cool dark place

QUESTIONS OR COMMENTS

www.Rxhomeo.com | 1.888.2796642 | info@rxhomeo.com
Rxhomeo, Inc 1504 Fairway Dr. Ste W 100 Lewisville, TX 75057 USA